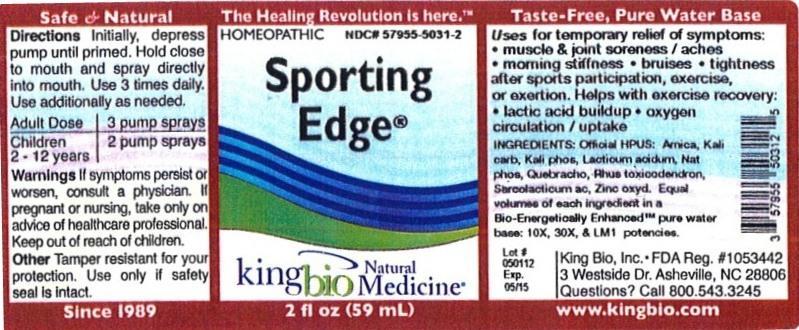 DRUG LABEL: Sporting Edge
NDC: 57955-5031 | Form: LIQUID
Manufacturer: King Bio Inc.
Category: homeopathic | Type: HUMAN OTC DRUG LABEL
Date: 20120720

ACTIVE INGREDIENTS: ARNICA MONTANA 10 [hp_X]/59 mL; POTASSIUM CARBONATE 10 [hp_X]/59 mL; POTASSIUM PHOSPHATE, DIBASIC 10 [hp_X]/59 mL; LACTIC ACID, DL- 10 [hp_X]/59 mL; SODIUM PHOSPHATE, DIBASIC, HEPTAHYDRATE 10 [hp_X]/59 mL; ASPIDOSPERMA QUEBRACHO-BLANCO BARK 10 [hp_X]/59 mL; TOXICODENDRON PUBESCENS LEAF 10 [hp_X]/59 mL; LACTIC ACID, L- 10 [hp_X]/59 mL; ZINC OXIDE 10 [hp_X]/59 mL
INACTIVE INGREDIENTS: WATER

Sporting Edge

Active Ingredients

Official HPUS: Arnica montana, Kali carbonicum, Kali phosphoricum, Lacticum acidum, natrum phosphoricum, Quebracho, Rhus toxicodendron, Sarcolacticum acidum, Zincum oxydatum.

Reference image sporting edge.jpg

Inactive Ingredient

Equal volumes of each ingredient in a Bio-Energetically Enhanced pure water base: 10X, 30X, and LM1potencies.

Reference image sporting edge.jpg

Purpose

Uses for temporary relief of symptoms:

- muscle and joint soreness / aches
- morning stiffness
- bruises
- tightness after sports participation, exercise, or exertion

Helps with exercise recovery:

- lactic acid buildup
- oxygen circulation / uptake

Reference image sporting edge.jpg

Dosage and Administration

Directions Initially, depress pump until primed. Hold close to mouth and spray directly into mouth. Use 3 times daily. Use additionally as needed.

Adult Dose 3 pump sprays

Children 2 - 12 years 2 pump sprays

Reference image sporting edge.jpg

Warnings

If symptoms persist or worsen, consult a physician. If pregnant or nursing, take only on advice of healthcare professional. Keep out of reach of children.

Other: Tamper resistant for your protection. Use only if safety seal is intact.

Reference image sporting edge.jpg

Keep out of reach of children.

Reference image sporting edge.jpg

Indications and Usage

For temporary relief of symptoms: muscle and joint soreness / aches, morning stiffness, bruises, tightness after sports participation, exercise, or exertion. Helps with exercise recovery: lactic acid buildup, oxygen circulation / uptake.

Reference image sporting edge.jpg

PACKAGE LABEL

King Bio Inc.

3 Westside Drive

Asheville, NC 28806

Questions? Call 800.543.3245

www.kingbio.com

Reference image sporting edge.jpg